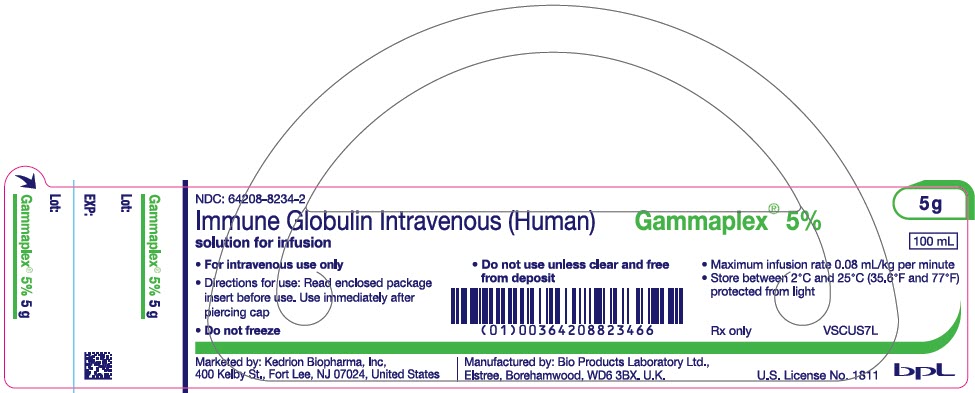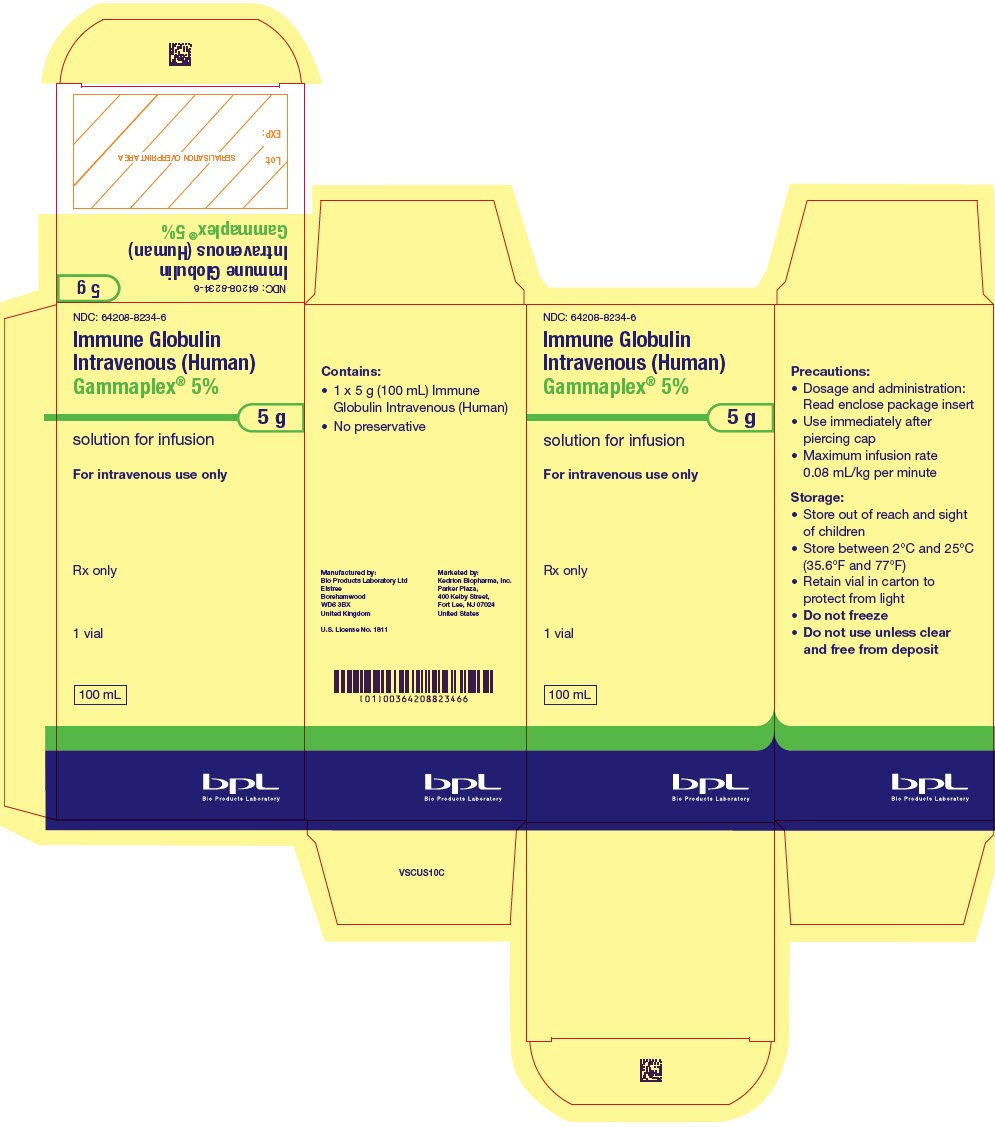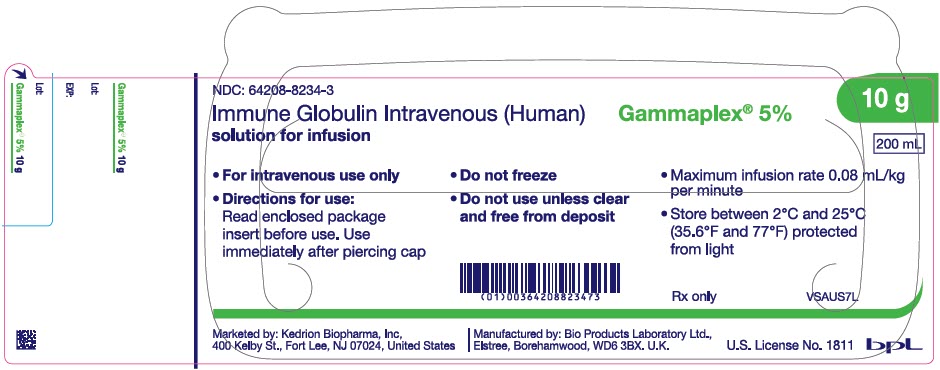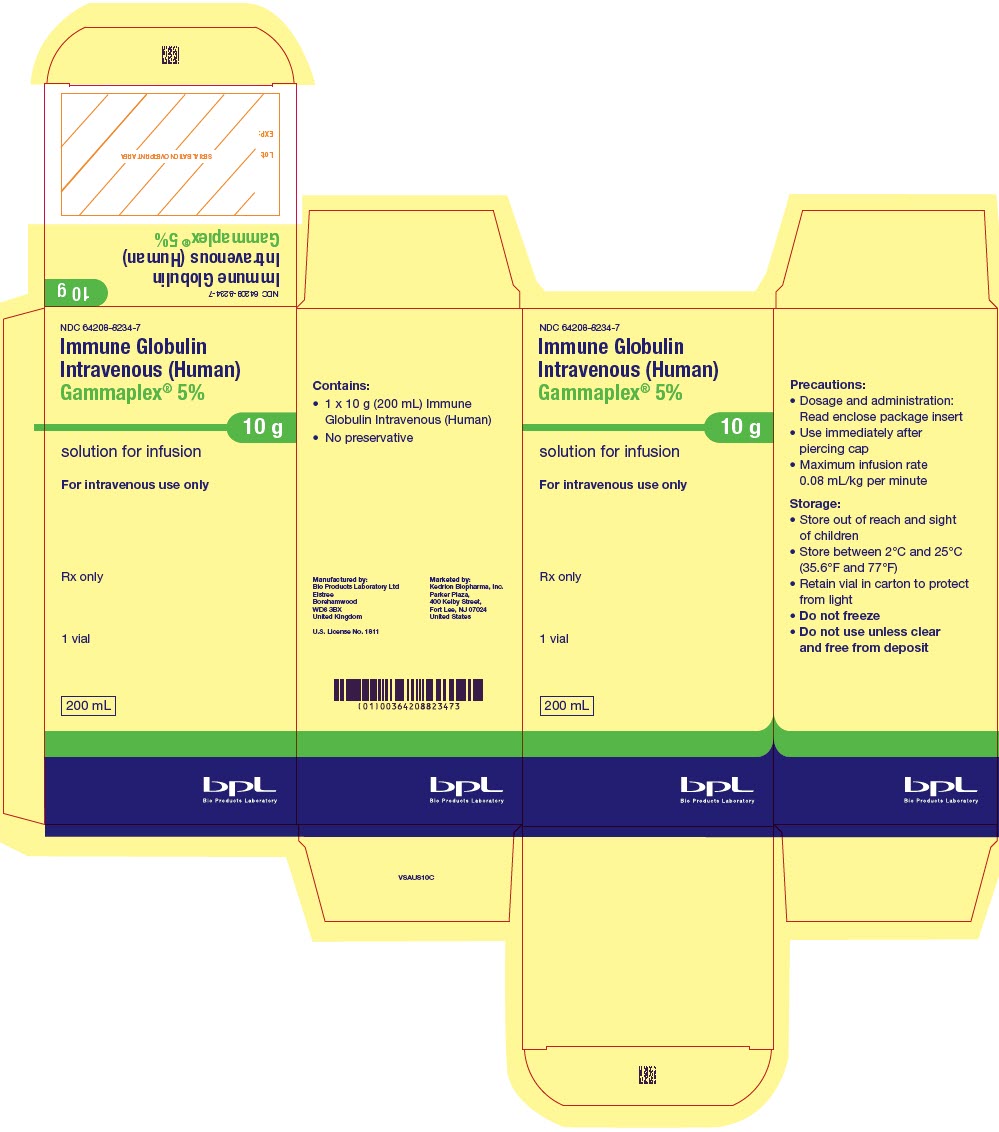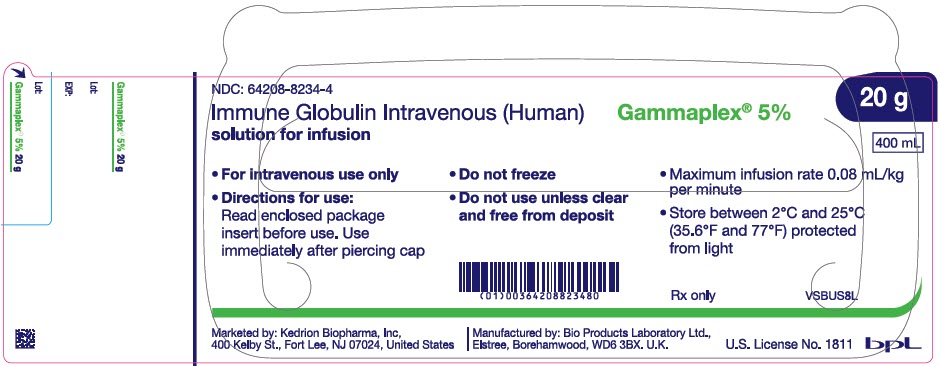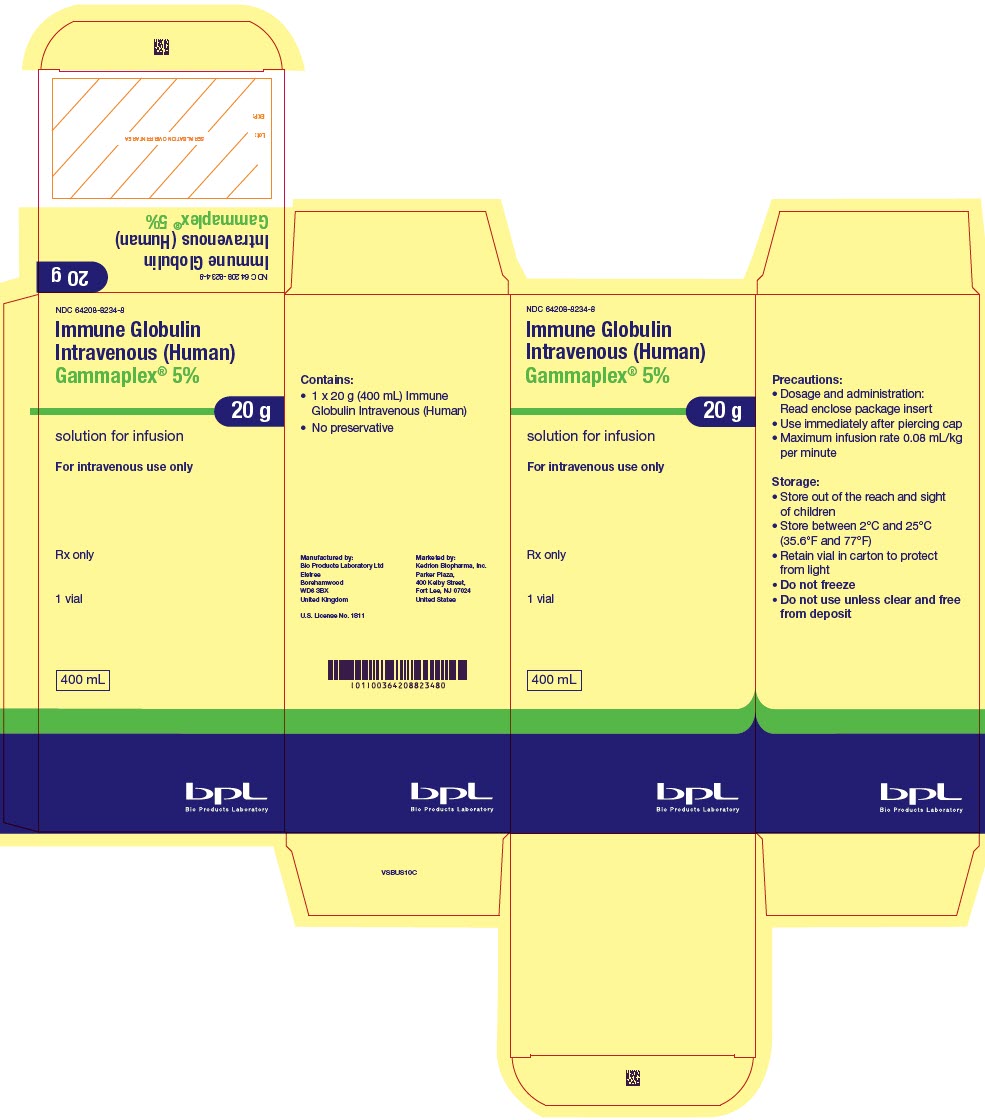 DRUG LABEL: Gammaplex
NDC: 64208-8234 | Form: SOLUTION
Manufacturer: Bio Products Laboratory Limited
Category: other | Type: PLASMA DERIVATIVE
Date: 20250916

ACTIVE INGREDIENTS: HUMAN IMMUNOGLOBULIN G 5 g/100 mL
INACTIVE INGREDIENTS: SORBITOL 5 g/100 mL; GLYCINE 0.6 g/100 mL; SODIUM CHLORIDE 0.3 g/100 mL; SODIUM ACETATE 0.2 g/100 mL; POLYSORBATE 80 5 g/100 mL

HIGHLIGHTS OF PRESCRIBING INFORMATION

These highlights do not include all the information needed to use GAMMAPLEX 5%® safely and effectively. See full prescribing information for GAMMAPLEX 5%®.
GAMMAPLEX 5% Immune Globulin Intravenous (Human), 5% Liquid, for intravenous use
Initial U.S. Approval: 2009

WARNING: THROMBOSIS, RENAL DYSFUNCTION and ACUTE RENAL FAILURE

See full prescribing information for complete boxed warning.

- Thrombosis may occur with immune globulin products, including GAMMAPLEX 5%. Risk factors may include: advanced age, prolonged immobilization, hypercoagulable conditions, history of venous or arterial thrombosis, use of estrogens, indwelling vascular catheters, hyperviscosity and cardiovascular risk factors (5.2).
- Renal dysfunction, acute renal failure, osmotic nephrosis, and death^1 may occur in predisposed patients with immune globulin intravenous (lGIV) products, including GAMMAPLEX 5%.
- Renal dysfunction and acute renal failure occur more commonly with IGIV products containing sucrose. GAMMAPLEX 5% does not contain sucrose (5.1).
- For patients at risk of thrombosis, renal dysfunction or acute renal failure, administer GAMMAPLEX 5% at the minimum dose and infusion rate practicable. Ensure adequate hydration in patients before administration. Monitor for signs and symptoms of thrombosis and assess blood viscosity in patients at risk for hyperviscosity (2.3, 5.1).

1 INDICATIONS AND USAGE

GAMMAPLEX 5% is an Immune Globulin Intravenous (Human) 5% Liquid indicated for the treatment of:

- primary humoral immunodeficiency (PI) in adults and pediatric patients 2 years of age and older (1.1)
- chronic immune thrombocytopenic purpura (ITP) (1.2)

2 DOSAGE AND ADMINISTRATION

For Intravenous Use Only

Indication | Dose | Initial infusion rate | Maintenance infusion rate (if tolerated)
PI | 300-800 mg/kg (6-16 mL/kg) every 3-4 weeks | 0.5 mg/kg/min (0.01 mL/kg/min) for 15 minutes | Increase gradually every 15 minutes to 4 mg/kg/min (0.08 mL/kg/min)
ITP | 1 g/kg (20 mL/kg) for 2 consecutive days | 0.5 mg/kg/min (0.01 mL/kg/min) for 15 minutes | Increase gradually every 15 minutes to 4 mg/kg/min (0.08 mL/kg/min)

- Ensure that patients with pre-existing renal insufficiency are not volume depleted; discontinue GAMMAPLEX 5% if renal function deteriorates (2.3, 5.1).
- For patients at risk of renal dysfunction, thrombotic events or volume overload, administer GAMMAPLEX 5% at the minimum infusion rate practicable (2.3, 5.1, 5.2, 5.8).

3 DOSAGE FORMS AND STRENGTHS

GAMMAPLEX 5% is a liquid solution containing 5% IgG (50 mg/mL).

4 CONTRAINDICATIONS

- History of anaphylactic or severe systemic reactions to human immunoglobulin (4).
- Patients with hereditary intolerance to fructose, also in infants and neonates for whom sucrose or fructose tolerance has not been established (4).
- IgA-deficient patients with antibodies against IgA and a history of hypersensitivity (4).

5 WARNINGS AND PRECAUTIONS

- IgA-deficient patients with antibodies to IgA are at greater risk of developing severe hypersensitivity and anaphylactic reactions (5.3).
- Hyperproteinemia, increased serum viscosity, and hyponatremia may occur in patients receiving IGIV therapy (5.4).
- Aseptic meningitis syndrome may occur, especially with high doses or rapid infusion (5.5).
- Hemolysis, either intravascular or due to enhanced red blood cell sequestration, can develop subsequent to GAMMAPLEX 5% treatments. Risk factors include high doses and non-O blood group. Closely monitor patients for hemolysis and hemolytic anemia (5.6).
- Monitor patients for pulmonary adverse reactions (transfusion-related acute lung injury [TRALI]) (5.7).
- Volume overload can occur. Monitor for signs and symptoms (5.8).
- Consider risks and benefits before prescribing the high dose regimen for chronic ITP in patients at risk of thrombosis, hemolysis, acute kidney injury, or volume overload (5).
- GAMMAPLEX 5% is made from human plasma and may contain infectious agents, e.g. viruses and, theoretically, the Creutzfeldt-Jakob disease agent (5.9).
- Passive transfer of antibodies may confound serologic testing (5.10).

6 ADVERSE REACTIONS

- PI - The most common adverse reactions reported in >5% of clinical trial subjects were headache, pyrexia, nasal congestion/edema, fatigue, nausea, hypertension, rash, hypotension, infusion site reaction, vomiting, myalgia, chills, tachycardia, chest pain/discomfort, pain, dizziness, malaise, dysuria, and dry skin (6).
- Chronic ITP - The most common adverse reactions reported in >5% of clinical trial subjects were headache, vomiting, nausea, pyrexia, pruritus, dehydration, and arthralgia (6).

To report SUSPECTED ADVERSE REACTIONS, contact Kedrion Biopharma, Inc. at 1-855-3KDRION (1-855-353-7466) or the FDA at 1-800-FDA-1088 or www.fda.gov/medwatch

7 DRUG INTERACTIONS

- Passive transfer of antibodies may transiently interfere with the immune response to live virus vaccines, e.g. measles, mumps, and rubella (7).
- Therapy with GAMMAPLEX 5% may confound serological testing (7).

8 USE IN SPECIFIC POPULATIONS

- Pregnancy: No human or animal data. Use only if clearly indicated (8.1).
- Geriatrics: In patients over the age of 65 or in any patient at risk of developing renal insufficiency, do not exceed the recommended dose and infuse GAMMAPLEX 5% at the minimum rate practicable (8.5).

FULL PRESCRIBING INFORMATION

WARNING: THROMBOSIS, RENAL DYSFUNCTION and ACUTE RENAL FAILURE

- Thrombosis may occur with immune globulin products, including GAMMAPLEX 5%. Risk factors may include: advanced age, prolonged immobilization, hypercoagulable conditions, history of venous or arterial thrombosis, use of estrogens, indwelling central vascular catheters, hyperviscosity and cardiovascular risk factors. Thrombosis may occur in the absence of known risk factors [see Warnings and Precautions (5.2), Patient Counseling Information (17)].
- Renal dysfunction, acute renal failure, osmotic nephrosis, and death may occur in predisposed patients who receive immune globulin intravenous (lGIV) products, including GAMMAPLEX 5%^1.
- Patients predisposed to renal dysfunction include those with any degree of pre-existing renal insufficiency, diabetes mellitus, age greater than 65 years, volume depletion, sepsis, paraproteinemia, or patients receiving known nephrotoxic drugs [see Warnings and Precautions (5.1)]. Renal dysfunction and acute renal failure occur more commonly in patients receiving IGIV products containing sucrose. GAMMAPLEX 5% does not contain sucrose.
- For patients at risk of thrombosis, renal dysfunction or acute renal failure, administer GAMMAPLEX 5% at the minimum dose and infusion rate practicable. Ensure adequate hydration in patients before administration. Monitor for signs and symptoms of thrombosis and assess blood viscosity in patients at risk for hyperviscosity [see Dosage and Administration (2.3), Warnings and Precautions (5.1)].

1 INDICATIONS AND USAGE

1.1 Primary Humoral Immunodeficiency (PI)

GAMMAPLEX 5% is an Immune Globulin Intravenous (Human), 5% Liquid indicated for replacement therapy in primary humoral immunodeficiency (PI) in adults and pediatric patients 2 years of age and older. This includes, but is not limited to, the humoral immune defect in common variable immunodeficiency, X-linked agammaglobulinemia (XLA), congenital agammaglobulinemia, Wiskott-Aldrich syndrome, and severe combined immunodeficiencies.

1.2 Chronic Immune Thrombocytopenic Purpura (ITP)

GAMMAPLEX 5% is indicated for the treatment of chronic immune thrombocytopenic purpura (ITP) to raise platelet counts.

2 DOSAGE AND ADMINISTRATION

For Intravenous Use Only

2.1 Dose

Table 1: Recommended Dosage and Administration for GAMMAPLEX 5%
Indication | Dose | Initial infusion rate | Maintenance infusion rate (if tolerated)
PI | 300-800 mg/kg (6-16 mL/kg) every 3-4 weeks | 0.5 mg/kg/min (0.01 mL/kg/min) for 15 minutes | Increase gradually every 15 minutes to 4 mg/kg/min (0.08 mL/kg/min)
ITP | 1 g/kg (20 mL/kg) for 2 consecutive days | 0.5 mg/kg/min (0.01 mL/kg/min) for 15 minutes | Increase gradually every 15 minutes to 4 mg/kg/min (0.08 mL/kg/min)

Treatment of Primary Humoral Immunodeficiency

As there are significant differences in the half-life of IgG among patients with PI, the frequency and amount of immunoglobulin therapy may vary from patient to patient. The proper amount can be determined by monitoring clinical response.

The recommended dose of GAMMAPLEX 5% for patients with PI is 300 to 800 mg/kg (6 to 16 mL/kg), administered every 3 to 4 weeks. If a patient has been exposed to measles, it may be prudent to administer an extra dose of Immune Globulin Intravenous as soon as possible and within 6 days of exposure. A dose of 400 mg/kg should provide a serum level > 240 mIU/mL of measles antibodies for at least two weeks. If a patient is at risk of future measles exposure and receives a dose of less than 530 mg/kg every 3-4 weeks, the dose should be increased to at least 530 mg/kg. This should provide a serum level of 240 mIU/mL of measles antibodies for at least 22 days after infusion. Adjust the dosage over time to achieve the desired serum trough levels and clinical response. If a patient misses a dose, administer the missed dose as soon as possible, and then resume scheduled treatments every 3 or 4 weeks, as applicable.

Treatment of Chronic Immune Thrombocytopenic Purpura

The recommended dose of GAMMAPLEX 5% for patients with ITP is 1 g/kg (20 mL/kg) on 2 consecutive days, providing a total dose of 2 g/kg. Carefully consider the relative risks and benefits before prescribing the high dose regimen (i.e. 1 g/kg/day for 2 days) in patients at increased risk of thrombosis, hemolysis, acute kidney injury, or volume overload [see Warnings and Precautions (5)]. Adequate data on the platelet response to the low dose regimen (e.g. 400 mg/kg per day for 5 consecutive days) are not available for GAMMAPLEX 5%.

2.2 Preparation and Handling

- GAMMAPLEX 5% is a clear or slightly opalescent, colorless or pale yellow liquid. Parenteral drug products should be inspected visually for particulate matter and discoloration prior to administration, whenever solution and container permit. Do not use if the solution is cloudy or turbid, or if it contains particulate matter.
- Do not freeze, and do not use any solution that has been frozen.
- Do not shake.
- GAMMAPLEX 5% should be at room temperature (up to 25°C [77°F]) at the time of administration.
- Do not use GAMMAPLEX 5% beyond the expiration date on the product label.
- The GAMMAPLEX 5% vial is for single use only. Due to the absence of anti-microbial preservatives, promptly administer GAMMAPLEX 5% after piercing the cap. Dispose of partially used or unused product.
- Infuse GAMMAPLEX 5% using a separate infusion line.
- Do not mix GAMMAPLEX 5% with other intravenous medications (including normal saline) or other IGIV products.
- An infusion pump may be used to control the rate of administration.
- If large doses of GAMMAPLEX 5% are to be administered, several vials may be pooled using aseptic technique. Begin infusion within 2 hours after pooling.

2.3 Administration

- Hydrate the patient adequately prior to the initiation of infusion.
- Due to the absence of anti-microbial preservatives, promptly administer GAMMAPLEX 5% after piercing the cap.
- Infuse GAMMAPLEX 5% intravenously using an intravenous infusion set. See Table 1 for recommended infusion rates.
- Monitor vital signs throughout the infusion.
- Slow or stop the infusion if adverse reactions occur.
- If symptoms subside, the infusion may be resumed at a lower rate that is comfortable for the patient.
- The observation time of patients after GAMMAPLEX 5% administration may vary. If the patient (a) has not received GAMMAPLEX 5% or another IgG product, (b) is switched from an alternative IGIV product or (c) has had a long interval since the previous infusion, prolong the observation time for adverse reactions after GAMMAPLEX 5% infusion.
- Certain severe adverse reactions may be related to the rate of infusion. Slowing or stopping the infusion often allows the reaction to disappear.
- Ensure that patients with pre-existing renal insufficiency are not volume depleted.
- For patients at increased risk of renal dysfunction, thrombotic events, or volume overload, administer GAMMAPLEX 5% at the minimum infusion rate practicable. Consider discontinuing GAMMAPLEX 5% administration if renal function deteriorates [see Boxed Warning, Warnings and Precautions (5.1, 5.2, 5.8)].

3 DOSAGE FORMS AND STRENGTHS

GAMMAPLEX 5% is a liquid solution containing 5% IgG (50 mg/mL).

4 CONTRAINDICATIONS

- GAMMAPLEX 5% is contraindicated in patients who have had an anaphylactic or severe systemic reaction to the administration of human immune globulin.
- GAMMAPLEX 5% is contraindicated in patients with hereditary intolerance to fructose, also in infants and neonates for whom sucrose or fructose tolerance has not been established.
- GAMMAPLEX 5% is contraindicated in IgA-deficient patients with antibodies to IgA and a history of hypersensitivity.

5 WARNINGS AND PRECAUTIONS

5.1 Renal Dysfunction/Failure

Acute renal dysfunction/failure, osmotic nephropathy, and death^1 may occur upon use of human IGIV products. Ensure that patients are not volume depleted before administering GAMMAPLEX 5%. In patients who are at risk of developing renal dysfunction, because of pre-existing renal insufficiency, predisposition to acute renal failure (such as diabetes mellitus, hypovolemia, overweight, use of concomitant nephrotoxic medicinal products or age >65 years), administer GAMMAPLEX 5% at the minimum infusion rate practicable [see Dosage and Administration (2.3)].

Periodic monitoring of renal function and urine output is particularly important in patients judged to be at increased risk of developing acute renal failure. Assess renal function, including measurement of blood urea nitrogen (BUN) and serum creatinine, before the initial infusion of GAMMAPLEX 5% and at appropriate intervals thereafter. If renal function deteriorates, consider discontinuing GAMMAPLEX 5%.

5.2 Thrombotic Events

Thrombosis may occur following treatment with immune globulin products, including GAMMAPLEX 5%^2. Risk factors may include: advanced age, prolonged immobilization, hypercoagulable conditions, history of venous or arterial thrombosis, use of estrogens, indwelling central vascular catheters, hyperviscosity and cardiovascular risk factors. Thrombosis may occur in the absence of known risk factors.

Consider baseline assessment of blood viscosity in patients at risk for hyperviscosity, including those with cryoglobulins, fasting chylomicronemia/markedly high triacylglycerols (triglycerides), or monoclonal gammopathies. For patients at risk of thrombosis, administer GAMMAPLEX 5% at the minimum dose and infusion rate practicable. Ensure adequate hydration in patients before administration. Monitor for signs and symptoms of thrombosis and assess blood viscosity in patients at risk for hyperviscosity [see Boxed Warning, Dosage and Administration (2.3), Patient Counseling Information (17)].

5.3 Hypersensitivity

Severe hypersensitivity reactions may occur [see Contraindications (4)]. In case of hypersensitivity, discontinue GAMMAPLEX 5% infusion immediately and institute appropriate treatment. Medications such as epinephrine should be available for immediate treatment of acute hypersensitivity reactions.

GAMMAPLEX 5% contains trace amounts of IgA (<10 micrograms/mL) [see Description (11)]. Patients with known antibodies to IgA may have a greater risk of developing potentially severe hypersensitivity and anaphylactic reactions. GAMMAPLEX 5% is contraindicated in patients with antibodies against IgA and a history of hypersensitivity reaction [see Contraindications (4)].

5.4 Hyperproteinemia, Increased Serum Viscosity, and Hyponatremia

Hyperproteinemia, increased serum viscosity, and hyponatremia may occur in patients receiving IGIV therapy. It is critical to clinically distinguish true hyponatremia from a pseudohyponatremia that is associated with or causally related to hyperproteinemia with concomitant decreased calculated serum osmolality or elevated osmolar gap, because treatment aimed at decreasing serum free water in patients with pseudohyponatremia may lead to volume depletion, a further increase in serum viscosity, and a possible predisposition to thrombotic events^2.

5.5 Aseptic Meningitis Syndrome (AMS)

AMS may occur with IGIV treatment. AMS usually begins within several hours to 2 days following IGIV treatment. Discontinuation of IGIV treatment has resulted in remission of AMS within several days without sequelae^3.

AMS is characterized by the following signs and symptoms: severe headache, nuchal rigidity, drowsiness, fever, photophobia, painful eye movements, nausea, and vomiting [see Patient Counseling Information (17)]. Cerebrospinal fluid (CSF) studies frequently reveal pleocytosis up to several thousand cells per cubic millimeter, predominantly from the granulocytic series, and elevated protein levels up to several hundred mg/dL, but negative culture results. Conduct a thorough neurological examination on patients exhibiting such signs and symptoms, including CSF studies, to rule out other causes of meningitis. AMS may occur more frequently in association with high doses (2 g/kg) and/or rapid infusion of IGIV.

5.6 Hemolysis

GAMMAPLEX 5% may contain blood group antibodies that can act as hemolysins and induce in vivo coating of red blood cells (RBCs) with immunoglobulin, causing a positive direct antiglobulin test (DAT) (Coombs' test) result and hemolysis^4. Delayed hemolytic anemia can develop subsequent to IGIV therapy due to enhanced RBC sequestration and acute hemolysis, consistent with intravascular hemolysis, has been reported^5. Cases of severe hemolysis-related renal dysfunction/failure or disseminated intravascular coagulation have occurred following infusion of IGIV.

The following risk factors may be associated with the development of hemolysis following IGIV administration: high doses (e.g. ≥2 g/kg), given either as a single administration or divided over several days, and non-O blood group^6. Other individual patient factors, such as an underlying inflammatory state (as may be reflected by, for example, elevated C-reactive protein or erythrocyte sedimentation rate), have been hypothesized to increase the risk of hemolysis following administration of IGIV^7, but their role is uncertain. Hemolysis has been reported following administration of IGIV for a variety of indications, including ITP and PI^4.

Closely monitor patients for clinical signs and symptoms of hemolysis, particularly patients with risk factors noted above. Consider appropriate laboratory testing in higher risk patients, including measurement of hemoglobin or hematocrit prior to infusion and within approximately 36 to 96 hours post infusion. If clinical signs and symptoms of hemolysis or a significant drop in hemoglobin or hematocrit have been observed, perform confirmatory laboratory testing. If transfusion is indicated for patients who develop hemolysis with clinically compromising anemia after receiving IGIV, perform adequate cross-matching to avoid exacerbating on-going hemolysis.

5.7 Transfusion-related Acute Lung Injury (TRALI)

Noncardiogenic pulmonary edema may occur in patients following IGIV treatment^8. TRALI is characterized by severe respiratory distress, pulmonary edema, hypoxemia, normal left ventricular function and fever. Symptoms typically appear within 1 to 6 hours following treatment.

Monitor patients for pulmonary adverse reactions. If TRALI is suspected, perform appropriate tests for the presence of anti-neutrophil antibodies in both the product and the patient's serum.

TRALI may be managed using oxygen therapy with adequate ventilatory support.

5.8 Volume Overload

Carefully consider the relative risks and benefits before prescribing the high dose regimen (for chronic ITP) in patients at increased risk of volume overload.

5.9 Transmissible Infectious Agents

GAMMAPLEX 5% is made from human blood, it may carry a risk of transmitting infectious agents, e.g. viruses, the variant Creutzfeldt-Jakob disease (vCJD) agent and, theoretically, the Creutzfeldt-Jakob disease (CJD) agent. No cases of transmission of viral diseases or CJD have been associated with the use of GAMMAPLEX 5%. All infections suspected by a physician possibly to have been transmitted by this product should be reported by the physician or other healthcare providers to Kedrion Biopharma, Inc. at 1-855-3KDRION (1-855-353-7466).

Before prescribing GAMMAPLEX 5%, the physician should discuss the risks and benefits of its use with the patient [see Patient Counseling Information (17)].

5.10 Laboratory Tests

- After infusion of immunoglobulin, the transitory rise of the various passively transferred antibodies in the patient's blood may yield positive serological testing results, with the potential for misleading interpretation.
- Passive transmission of antibodies to erythrocyte antigens (e.g. A, B, and D) may cause a positive direct or indirect antiglobulin (Coombs') test.
- Clinically assess patients with known renal dysfunction, diabetes mellitus, age greater than 65 years, volume depletion, sepsis, paraproteinemia, or those receiving nephrotoxic agents, and monitor as appropriate (BUN, serum creatinine, urine output) during therapy with GAMMAPLEX 5%.
- Consider baseline assessment of blood viscosity in patients at risk for hyperviscosity, including those with polycythemia, cryoglobulins, fasting chylomicronemia/markedly high triglycerides, or monoclonal gammopathies.
- Consider measuring hemoglobin or hematocrit at baseline and approximately 36 to 96 hours post infusion in patients at higher risk of hemolysis. If signs and/or symptoms of hemolysis are present after an infusion of GAMMAPLEX 5%, perform appropriate laboratory testing for confirmation.
- If TRALI is suspected, perform appropriate tests for the presence of anti-neutrophil antibodies in both the product and patient's serum.

6 ADVERSE REACTIONS

Serious adverse reactions (ARs) observed in clinical trial subjects with primary humoral immunodeficiency (PI) were thrombosis and chest pain. The one event of thrombosis (1 subject, 2%) was reported in an adult who also had a diagnosis of antiphospholipid syndrome which results in increased clotting tendency [see Warnings and Precautions (5.2)].

Serious ARs observed in clinical trial subjects with immune thrombocytopenic purpura (ITP) were headache, vomiting and dehydration. In addition following a review of the data, 4 subjects (11%) were considered to have experienced asymptomatic suspected treatment-emergent hemolysis [see Clinical Trials Experience (6.1)].

The following potential serious ARs are described above and/or elsewhere in the labeling:

- Thrombotic Events [see Warnings and Precautions (5.2)]
- Hemolysis [see Warnings and Precautions (5.6)]

The most common ARs observed in the PI clinical trials were headache (29 subjects, 39%), pyrexia (11 subjects, 15%), nasal congestion/edema (10 subjects, 13%), fatigue (9 subjects, 12%), nausea (7 subjects, 9%), hypertension (6 subjects, 8%), rash (6 subjects, 8%), hypotension (5 subjects, 7%), infusion site reactions (5 subjects, 7%), vomiting (5 subjects, 7%), myalgia (4 subjects, 5%), chills (4 subjects, 5%), tachycardia (4 subjects, 5%), chest pain/discomfort (4 subjects, 5%), pain (4 subjects, 5%), dizziness (4 subjects, 5%), malaise (4 subjects, 5%), dysuria (4 subjects, 5%), and dry skin (4 subjects, 5%).

The most common ARs observed in the chronic ITP clinical trial were headache (12 subjects, 34%), vomiting (8 subjects, 23%), nausea (5 subjects, 14%), pyrexia (5 subjects, 14%), pruritus (2 subjects, 6%) and arthralgia (2 subjects, 6%).

6.1 Clinical Trials Experience

As clinical trials are conducted under widely varying conditions, adverse reaction rates observed in the clinical trials of a drug cannot be directly compared to rates in the clinical trials of another drug and may not reflect the rates observed in clinical practice.

Primary Humoral Immunodeficiency Study

In a multicenter, open-label, non-randomized clinical trial, 50 subjects with primary humoral immunodeficiency received doses of GAMMAPLEX 5% ranging from 279 to 799 mg/kg every 21 days (mean dose 465 mg/kg) or 28 days (mean dose 458 mg/kg), for up to 12 months [see Clinical Studies (14.1)].

Twenty-four subjects (48%) had an AR at some time during the clinical trial that was considered product-related. Of these 24 subjects, three had ARs that were considered definitely related to GAMMAPLEX 5% including headache, pyrexia, tachycardia, chest discomfort, and hypertension. More subjects with the 21-day infusion cycle had at least one AR (14 of 22 subjects, 64%) than subjects with the 28-day infusion cycle (10 of 28 subjects, 36%). The total number of ARs during infusion or within 72 hours of infusion was 237 (a rate of 0.34 ARs per infusion), reflecting that some subjects experienced more than one AR during the observation period. The percentage of GAMMAPLEX 5% infusions with one or more ARs within 72 hours of infusion was 21%. The upper bound of the 1-sided 95% confidence interval for this percentage was 24%, which was below the pre-specified upper limit of 40% for this safety endpoint.

The most common ARs observed in this clinical trial were headache (18 subjects, 36%), fatigue (6 subjects, 12%), nausea (6 subjects, 12%), pyrexia (6 subjects, 12%), pain (4 subjects, 8%), hypertension (3 subjects, 6%), chills (3 subjects, 6%), myalgia (3 subjects, 6%) and vomiting (3 subjects, 6%). Two subjects experienced serious ARs (thrombosis and chest pain).

Forty-seven of the 50 subjects enrolled in this clinical trial had a negative direct antiglobulin test (DAT) at baseline. Of these 47 subjects, 4 (9%) developed a positive DAT at some time during the clinical trial. However, no subjects showed evidence of hemolytic anemia.

There was no evidence of transmission of hepatitis B virus (HBV), hepatitis C virus (HCV), human immunodeficiency virus (HIV) or parvovirus B19 during this clinical trial.

Table 2: Adverse Reactions (ARs) Occurring in >5% of Subjects with PI
Adverse Reactions | Subjects (%) | Infusions (%)
PI studies | PI [n=75] | PI [n=1071]
Headache | 29 (39%) | 74 (6.9%)
Sinusitis | 14 (19%) | 17 (1.6%)
Pyrexia | 11 (15%) | 13 (1.2%)
Nasal congestion/edema | 10 (13%) | 8 (0.7%)
Fatigue | 9 (12%) | 13 (1.2%)
Nausea | 7 (9%) | 8 (0.7%)
Hypertension | 6 (8%) | 8 (0.7%)
Upper respiratory tract infection | 6 (8%) | 8 (0.7%)
Rash | 6 (8%) | 6 (0.6%)
Hypotension | 5 (7%) | 11 (1.0%)
Infusion site reaction | 5 (7%) | 6 (0.6%)
Vomiting | 5 (7%) | 4 (0.4%)
Myalgia | 4 (5%) | 15 (1.4%)
Chills | 4 (5%) | 9 (0.8%)
Tachycardia | 4 (5%) | 6 (0.6%)
Rhinitis | 4 (5%) | 6 (0.6%)
Chest pain/discomfort | 4 (5%) | 5 (0.5%)
Pain | 4 (5%) | 5 (0.5%)
Dizziness/vertigo | 4 (5%) | 4 (0.4%)
Malaise/asthenia/lethargy | 4 (5%) | 4 (0.4%)
Dysuria/cystitis/UTI | 4 (5%) | 4 (0.4%)
Dry skin/eczema | 4 (5%) | 4 (0.4%)
Bronchitis | 4 (5%) | 4 (0.4%)

Table 3: ARs [Adverse Reactions (ARs) are defined as treatment emergent adverse events which met any of the following criteria: (a) adverse events which began during an infusion of GAMMAPLEX 5% or within 72 hours of the end of an infusion, (b) adverse events considered by the investigator or sponsor to have been possibly, probably, or definitely related to administration of GAMMAPLEX 5%, (c) adverse events for which the investigator's causality assessment was either missing or indeterminate.] in >5% of Pediatric Subjects with PI [ARs are presented for the PI studies if occurred in >5% of subjects. ARs seen in the pediatric study are presented in a separate table if occurred in >5% of pediatric subjects and were not reported in the major effectiveness study.]
Adverse Reactions PI Pediatric | Subjects (%) | Infusions (%)
Adverse Reactions PI Pediatric | PI [n=25] | PI [n=368]
Dyspnea | 2 (8%) | 2 (0.5%)
Otitis media acute | 2 (8%) | 2 (0.5%)
Tonsillar disorder | 2 (8%) | 2 (0.5%)

Pediatric Primary Humoral Immunodeficiency Study

In a multicenter, open-label, non-randomized clinical trial, 25 children and adolescents with primary humoral immunodeficiency received doses of GAMMAPLEX 5% ranging from 300 to 800 mg/kg every 21 days (mean dose 545 mg/kg) or 28 days (mean dose 521 mg/kg), for up to 12 months [see Clinical Studies (14.1)].

Fourteen subjects (56%) had an AR at some time during the clinical trial that was considered product-related. Of these 14 subjects, two had ARs that were considered definitely related to GAMMAPLEX 5% including headache, fatigue and myalgia. Seven subjects with the 21-day infusion cycle had at least one AR (7 of 14 subjects, 50%), as did seven subjects with the 28-day infusion cycle (7 of 11 subjects, 64%).

Chronic Immune Thrombocytopenic Purpura Study

In a multicenter, open-label, non-randomized clinical trial, 35 subjects with chronic immune thrombocytopenic purpura were treated with a nominal dose of 1,000 mg/kg on each of two consecutive days (total dose 2,000 mg/kg). Doses of GAMMAPLEX 5% ranged from 482 to 1149 mg/kg on an infusion day. The median total dose per subject was 2035 mg/kg. Pre-medication with antihistamine or analgesic drugs was permitted if required, but corticosteroids were not permitted prior to infusion as pre-medication. Ten subjects received corticosteroids for ITP during the trial and one additional subject received corticosteroids as pre-medication in violation of the protocol. All 35 subjects received at least one infusion of clinical trial drug, and all but one subject completed the first course of treatment.

Twenty-four subjects (69%) reported at least one AR (103 in total); the most commonly reported being headache (12 subjects, 34%), vomiting (8 subjects, 23%), nausea (5 subjects, 14%), pyrexia (5 subjects, 14%), pruritus (2 subjects, 6%), dehydration (2 subjects, 6%) and arthralgia (2 subjects, 6%). Three subjects experienced a total of five serious ARs. Of the five serious ARs, one subject had three concurrently (vomiting, dehydration and headache) and two subjects each had one serious AR (headache). One of these latter two subjects discontinued from the clinical trial because of the severe headache. Table 4 lists the ARs in more than 5% of subjects.

Based on a review of clinical and laboratory data, 4/35 subjects (11%) with drops in hemoglobin exceeding 2 g/dL following administration of GAMMAPLEX 5% were considered to have experienced suspected treatment-emergent hemolysis. Milder treatment-emergent hemolysis could not be excluded for an additional 7 subjects, giving a total of 11 of 35 subjects (31%) for whom hemolysis could not be excluded (not including an additional two subjects who lacked follow-up testing for hemolysis, so their hemolysis status was considered unassessable). Data for two subjects were consistent with possible intravascular hemolysis, including one subject who may also have had an element of extravascular hemolysis. Nine of the possible hemolysis cases were mild and appeared consistent with possible extravascular hemolysis.

There was no evidence of transmission of HBV, HCV, HIV and parvovirus B19 during this clinical trial.

Table 4: Adverse Reactions (ARs [Adverse Reactions (ARs) are defined as treatment emergent adverse events which met any of the following criteria: (a) adverse events which began during an infusion of GAMMAPLEX 5% or within 72 hours of the end of an infusion, (b) adverse events considered by the investigator or sponsor to have been possibly, probably, or definitely related to administration of GAMMAPLEX 5%, (c) adverse events for which the investigator's causality assessment was either missing or indeterminate.]) Occurring in >5% of Subjects with ITP
Adverse Reactions | Subjects (%) | Infusions (%)
Adverse Reactions | ITP [n=35] | ITP [n=94]
Headache | 12 (34%) | 15 (16%)
Vomiting | 8 (23%) | 9 (9.6%)
Nausea | 5 (14%) | 5 (5.3%)
Pyrexia | 5 (14%) | 7 (7.4%)
Pain | 2 (6%) | 2 (2.1%)
Abdominal pain upper | 2 (6%) | 2 (2.1%)
Gastritis | 2 (6%) | 2 (2.1%)
Contusion | 2 (6%) | 2 (2.1%)
Arthralgia | 2 (6%) | 2 (2.1%)
Cough | 2 (6%) | 2 (2.1%)
Anemia | 2 (6%) | 1 (1.1%)
Ecchymosis | 2 (6%) | 3 (3.2%)
Pruritus | 2 (6%) | 2 (2.1%)
Dehydration | 2 (6%) | 2 (2.1%)
Hypertension | 2 (6%) | 1 (1.1%)
Neck pain | 2 (6%) | 1 (1.1%)

6.2 Postmarketing Experience

As adverse reactions are voluntarily reported post-approval from a population of uncertain size, it is not always possible to reliably estimate their frequency or establish a causal relationship to product exposure.

In addition to the adverse reactions identified in clinical studies [see Adverse Reactions (6.1)], the following adverse reactions have been identified during postmarketing use of GAMMAPLEX 5%:

- Infusion reactions: Dizziness
- Respiratory: Pulmonary embolism, dyspnea, respiratory distress
- Cardiovascular: Myocardial infarction, other thromboembolic event
- Neurological: Migraine, aseptic meningitis
- Integumentary: Rash, urticaria
- Musculoskeletal: Musculoskeletal pain

The following adverse reactions have been identified during postmarketing use of intravenous immune globulins^9:

- Infusion reactions: Hypersensitivity (e.g. anaphylaxis), headache, diarrhea, tachycardia, fever, fatigue, dizziness, malaise, chills, flushing, urticaria or other skin reactions, wheezing or other chest discomfort, nausea, vomiting, rigors, back pain, myalgia, arthralgia, and changes in blood pressure
- Renal: Acute renal dysfunction/failure, osmotic nephropathy
- Respiratory: Apnea, Acute Respiratory Distress Syndrome (ARDS), TRALI, cyanosis, hypoxemia, pulmonary edema, dyspnea, bronchospasm
- Cardiovascular: Cardiac arrest, thromboembolism, vascular collapse, hypotension
- Neurological: Coma, loss of consciousness, seizures, tremor, aseptic meningitis syndrome
- Integumentary: Stevens-Johnson syndrome, epidermolysis, erythema multiforme, dermatitis (e.g. bullous dermatitis)
- Hematologic: Pancytopenia, leukopenia, hemolysis, positive direct antiglobulin (Coombs') test
- Gastrointestinal: Hepatic dysfunction, abdominal pain
- General/Body as a Whole: Pyrexia, rigors

7 DRUG INTERACTIONS

- Transitory rise of the various passively transferred antibodies in the patient's blood after infusion of immunoglobulin may yield positive serological testing results, with the potential for misleading interpretation. Passive transmission of antibodies to erythrocyte antigens (e.g. A, B, and D) may cause a positive direct or indirect antiglobulin (Coombs') test.
- Passive transfer of antibodies may transiently interfere with the immune response to live virus vaccines such as measles, mumps, rubella and varicella^(10, 11). Inform the immunizing physician of recent therapy with GAMMAPLEX 5% so that appropriate measures may be taken [see Patient Counseling Information (17)].

8 USE IN SPECIFIC POPULATIONS

8.1 Pregnancy

Risk Summary

Animal reproduction studies have not been conducted with GAMMAPLEX 5%. It is also not known whether GAMMAPLEX 5% can cause fetal harm when administered to a pregnant woman or can affect reproduction capacity. GAMMAPLEX 5% should be given to a pregnant woman only if clearly needed. Immunoglobulins cross the placenta from maternal circulation increasingly after 30 weeks of gestation.^12

8.2 Lactation

Risk Summary

Use of GAMMAPLEX 5% has not been evaluated in nursing mothers.

8.4 Pediatric Use

Treatment of Primary Humoral Immunodeficiency

GAMMAPLEX 5% was evaluated in six pediatric patients with primary humoral immunodeficiency in one study (2 between ages of 9 and 10, and 4 between ages 12 and 16), and 25 patients in a second study (3 between ages of 2 to 5, 12 between ages of 6 to 11, and 10 between ages of 12 to 16). No pediatric-specific dose requirements were necessary to achieve the desired serum IgG levels [see Clinical Studies (14)].

Safety and efficacy of GAMMAPLEX 5% was not evaluated and established in pediatric patients below the age of 2 years.

Fourteen subjects (56%) had an AR at some time during the pediatric clinical trial that was considered product-related. Of these 14 subjects, two had ARs that were considered definitely related to GAMMAPLEX 5% including headache, fatigue and myalgia. Seven subjects with the 21-day infusion cycle had at least one AR (7 of 14 subjects, 50%), as did seven subjects with the 28-day infusion cycle (7 of 11 subjects, 64%).

Treatment of Chronic Immune Thrombocytopenic Purpura

GAMMAPLEX 5% was evaluated in three pediatric subjects with chronic immune thrombocytopenic purpura (two aged 6 and one aged 12). This number of pediatric patients was too small for separate evaluation from the adult patients for efficacy, however 31 pediatric patients have received GAMMAPLEX 5% in the PI studies demonstrating safety in this population [see Clinical Studies (14)].

8.5 Geriatric Use

Use caution when administering GAMMAPLEX 5% to patients aged 65 years and over who are judged to be at increased risk of developing renal insufficiency or thrombotic events [see Boxed Warning, Warnings and Precautions (5.1, 5.2)]. Do not exceed recommended doses, and administer GAMMAPLEX 5% at the minimum infusion rate practicable.

Eight patients with primary humoral immunodeficiency at or over the age of 65 years were included within the clinical evaluation of GAMMAPLEX 5%. This number of geriatric patients was too small for separate evaluation from the younger patients for safety or efficacy [see Clinical Studies (14)].

10 OVERDOSAGE

Overdosage may lead to fluid overload and hyperviscosity, particularly in the elderly and in patients with renal impairment.

11 DESCRIPTION

GAMMAPLEX 5% is a ready-to-use sterile solution of polyclonal human Immunoglobulin G for intravenous administration that contains sorbitol, glycine and polysorbate 80 as stabilizers. Specifically, GAMMAPLEX 5% contains approximately 5 g normal human immunoglobulin and 5 g D-sorbitol in 100 mL of buffer solution containing: 0.6 g glycine, 0.2 g sodium acetate, 0.3 g sodium chloride and about 5 mg polysorbate 80. Immunoglobulin G purity is > 95%, the pH is in the range of 4.8 to 5.1, and osmolality is not less than 240 mOsmol/kg (typically 420 to 500 mOsmol/kg). The distribution of the four IgG subclasses is approximately 64% IgG1, 30% IgG2, 5% IgG3, and 1% IgG4. The content of IgA is lower than 10 micrograms/mL. The anti-D and anti-A/anti-B hemagglutinin content of the drug product is strictly controlled to specification. GAMMAPLEX 5% contains no reducing carbohydrate stabilizers (e.g. sucrose, maltose) and no preservative.

GAMMAPLEX 5% is prepared from large pools of human plasma by a combination of cold ethanol fractionation and ion exchange chromatography. Fab functions tested include antigen binding activity, and Fc functions tested include complement activation and rubella antibody-mediated hemolysis.

GAMMAPLEX 5% is manufactured from plasma, obtained from healthy US donors, who have passed viral screening tests. All donors are subjected to medical examinations, laboratory tests, and a review of their medical history before being allowed to donate blood or plasma.

All plasma donations are screened for antibody to HIV-1/2 and hepatitis C virus (HCV), and hepatitis B surface antigen (HBsAg). Additional testing of donations is carried out in plasma mini-pools (512 donations per pool) that undergo nucleic acid amplification testing (NAT) for HIV, hepatitis B virus (HBV), HCV, hepatitis A virus (HAV) and parvovirus B19.

Further testing is carried out on the manufacturing pools for HBsAg, and antibody to HIV-1/2; HCV and parvovirus B19 are also tested by NAT, with the limit for B19 set to not exceed 10^4 IU B19 DNA per mL plasma.

There are three processing steps specifically designed to remove or inactivate viruses:

1) Solvent/Detergent treatment is targeted to enveloped viruses;

2) A virus filtration step designed to remove small viruses including non-enveloped viruses, on a size exclusion basis; and

3) The terminal low pH incubation step is identified as contributing to the overall viral clearance capacity for enveloped and non-enveloped viruses.

The capacity of the manufacturing process to remove and/or inactivate enveloped and non-enveloped viruses has been validated by laboratory spiking studies on a scaled down process model. Overall virus reduction was calculated only from steps that were mechanistically independent from each other.

In addition, each step was validated to provide robust virus reduction. The table below presents the contribution of each process step to virus reduction and the overall process reduction.

Table 5: Viral Reduction by Process Step
Virus | Type (Envelope/Genome) | Size (nm) | Process Log10 Reduction of Virus (LRV) over manufacturing step
Virus | Type (Envelope/Genome) | Size (nm) | Solvent Detergent | 20 nm filtration | Terminal low pH/elevated temperature incubation | Total LRV
HIV | Env/RNA | 80-100 | >6.8 | I | >6.1 | >12.9
SIN | Env/RNA | 70 | >6.7 | 6.2 | >7.3 | >20.2
WNV | Env/RNA | 50 | >6.4 | I | NT | >6.4
BVDV | Env/RNA | 40-60 | >5.6 | I | >6.1 | >11.7
IBR | Env/DNA | 200 | >5.0 | I | >6.3 | >11.3
HAV | Non-Env/RNA | 30 | NA | >4.8 | 0.9 | >4.8
EMC | Non-Env/RNA | 30 | NA | >4.8 | 1.6 | >6.4
CPV | Non-Env/RNA | 18-24 | NA | 3.2 | 1.1 | 4.3
HIV: | Human immunodeficiency virus
SIN: | Sindbis virus, model for hepatitis C virus (HCV)
WNV: | West Nile Virus
BVDV: | Bovine viral diarrhea virus, model for HCV
IBR: | Infectious bovine rhinotracheitis, bovine herpes virus model for enveloped DNA viruses including hepatitis B
HAV: | Hepatitis A virus
EMC: | Encephalomyocarditis, model for HAV
CPV: | Canine parvovirus, model for human parvovirus B19
NA: | Not applicable, solvent detergent step is limited to the inactivation of enveloped viruses
I: | Inactivation by the product intermediate precluded the accurate estimation of the removal of these viruses by the filtration step
NT: | Not tested
B19: | Viral clearance of human parvovirus B19 was investigated experimentally at the 20 nm filtration step. The estimated Log reduction Factor obtained was 6.0

12 CLINICAL PHARMACOLOGY

12.1 Mechanism of Action

Treatment of Primary Humoral Immunodeficiency - GAMMAPLEX 5% is a replacement therapy for primary humoral immunodeficiency. It acts through a broad spectrum of opsonic and neutralizing IgG antibodies against pathogens and their toxins involving antigen binding and effector functions^13,14. However, the mechanism of action in PI has not been fully elucidated.

Treatment of Chronic Immune Thrombocytopenic Purpura - The mechanism of action of high doses of immunoglobulins in the treatment of chronic ITP has not been fully elucidated.

12.3 Pharmacokinetics

Treatment of Primary Humoral Immunodeficiency

In the major effectiveness study assessing safety and efficacy in primary humoral immunodeficiency, the pharmacokinetics (PK) of GAMMAPLEX 5% was assessed after administration to 24 subjects on 21- or 28-day infusion cycles. Blood samples for PK analysis were obtained after Infusion 9 for subjects on a 21-day schedule (9 subjects) and after Infusion 7 for subjects on a 28-day schedule (15 subjects), i.e. during the sixth month after initiation of GAMMAPLEX 5% treatment.

The mean dose (range) for those on the 21-day schedule was 476 mg/kg (330 to 721 mg/kg), and 468 mg/kg (324 to 799 mg/kg) for those on the 28-day schedule. Table 6 summarizes the PK parameters of GAMMAPLEX 5%, measured as serum concentrations of total IgG.

In a separate pediatric clinical trial assessing safety and efficacy in pediatric primary humoral immunodeficiency, the pharmacokinetics (PK) of GAMMAPLEX 5% was assessed after administration to 23 subjects on 21- or 28-day infusion cycles. Blood samples for PK analysis were obtained after Infusion 9 for subjects on a 21-day schedule (13 subjects) and after Infusion 7 for subjects on a 28-day schedule (10 subjects), i.e. during the sixth month after initiation of GAMMAPLEX 5% treatment.

The mean dose (range) for the 21-day interval was 545 mg/kg (429 - 689 mg/kg), and 521 mg/kg (316- 800 mg/kg) for those on the 28-day schedule. Table 6 summarizes the PK parameters of GAMMAPLEX 5%, measured as serum concentrations of total IgG.

Table 6: Pharmacokinetic Parameters of GAMMAPLEX 5% in Subjects with PI (corrected for baseline concentration)
Indication: | PI Adult study |  | PI Pediatric Study [: 23 out of 25 subjects were analyzed.]
Parameter (unit) | 21-day Dosing Interval (n=9) | 28-day Dosing Interval (n=14) | 2-5 years (n=3) | 6-11years (n=11) | 12-16 years (n=9)
Parameter (unit) | Mean [Geometric mean] (95% confidence intervals) | Mean (95% confidence intervals) | Mean (95% confidence intervals) | Mean (95% confidence intervals) | Mean (95% confidence intervals)
Cmax (mg/dL) | 1060 (867-1290) | 1190 (995-1410) | 864 (619-1210) | 917 (718-1170) | 976 (760-1250)
Tmax (hr) | 3.33 (NC) | 3.30 (NC) | 3.98 (NC) | 3.85 (NC) | 4.08 (NC)
AUC (days mg/dL) | 6280 [AUC0-tau, tau = dosing interval] (5080-7760) | 8770 (7540-10200) | 6210 (4000-9650) | 6420 (4940-8350) | 7240 (5790-9050)
Half-Life (days) | 6.06 (4.89-7.50) | 5.79 (4.94-6.78) | 4.97 (3.82-6.46) | 5.08 (4.09-6.31) | 5.45 (4.60-6.47)
Clearance (dL/days/kg) | 0.073 (0.061-0.088) | 0.053 (0.046-0.061) | 0.096 (0.063-0.147) | 0.082 (0.068-0.098) | 0.072 (0.057-0.09)
Volume of Distribution (dL/kg) | 0.60 (0.46-0.78) | 0.43 (0.39-0.48) | 0.70 (0.40-1.23) | 0.62 (0.43-0.89) | 0.55 (0.43-0.71)
NC – Not Calculated

14 CLINICAL STUDIES

14.1 Treatment of Primary Humoral immunodeficiency

Major Effectiveness study

In a Phase 3 multicenter, open-label clinical trial to evaluate the efficacy, safety, and pharmacokinetics of GAMMAPLEX 5% in primary humoral immunodeficiency, 50 subjects on regular IGIV replacement therapy for at least 3 months prior to participation were treated for 12 months at 21-day (22 subjects) or 28-day (28 subjects) dosing intervals. Of the 50 subjects, 26 were male and 24 were female, and 46 were Caucasian. They were in the age range of 9 to 78 years.

Doses ranged from 279 mg/kg to 799 mg/kg. The mean dose (range) for the 21-day interval was 465 mg/kg (330 - 693 mg/kg); the mean dose (range) for the 28-day interval was 458 mg/kg (326 - 790 mg/kg). Subjects received a total of 703 infusions of GAMMAPLEX 5%. The maximum infusion rate allowed during this clinical trial was 0.08 mL/kg/min (4 mg/kg/min).

The efficacy analysis was based on the annual rate of acute serious bacterial infections (SABIs), defined as pneumonia, bacteremia/septicemia, osteomyelitis/septic arthritis, visceral abscess, and bacterial meningitis, per subject per year^15. Other efficacy analyses were based on the annual rate of infections, antibiotic use, days out of work/school/day care or unable to perform normal activities due to illness, and days of hospitalization.

During the 12-month clinical trial period, no serious acute bacterial infections occurred in any subject with an onset date between the first infusion of GAMMAPLEX 5% and the first follow-up visit, inclusive. Thus, the mean event rate of serious, acute, bacterial infections per year was zero (with an upper 1-sided 99% confidence interval of 0.101).

Table 7: Summary of Efficacy Results in Subjects with PI
Clinical Analyses for Efficacy | Number of Subjects | 50
Clinical Analyses for Efficacy | Total Number of Subject Days | 16715
Infections | Annual rate of confirmed serious acute bacterial infections [Defined as pneumonia, bacterial meningitis, bacteremia/septicemia, osteomyelitis/septic arthritis, and visceral abscess.] | 0/subject year [Upper 1-sided 99% confidence interval: 0.101]
Infections | Annual rate of other infections (median) | 3.07 infections/subject year
Antibiotic use (therapeutic) | Number of subjects (%) | 40 (80%)
Antibiotic use (therapeutic) | Annual rate | 47.2 days/subject year
Out of work/school/day care or unable to perform normal activities due to illness | Number of subjects (%) | 23 (46%)
Out of work/school/day care or unable to perform normal activities due to illness | Number of days (%) | 394 (2.36%)
Out of work/school/day care or unable to perform normal activities due to illness | Annual rate | 8.73 days/subject year
Hospitalization | Number of subjects (%) | 4 (8%)
Hospitalization | Number of days (%) | 29 (0.17%)
Hospitalization | Annual rate | 0.75 days/subject year
Duration of exposure in all tables relating to the major effectiveness study was calculated as the difference between the date of the last visit (first follow-up visit) i.e. approximately 10-14 days following the last dose of GAMMAPLEX 5% and the date of the first GAMMAPLEX 5% infusion (plus one day).

Pediatric study

In a multicenter, open-label clinical trial to evaluate the efficacy, safety, and pharmacokinetics of GAMMAPLEX 5% in primary humoral immunodeficiency in children and adolescents, 25 subjects on regular IGIV replacement therapy for at least 3 months prior to participation were treated for 12 months at 21-day (14 subjects) or 28-day (11 subjects) dosing intervals. Of the 25 subjects, 19 were male and 6 were female, and all were Caucasian in the age range of 3 to 16 years.

Doses ranged from 300 mg/kg to 800 mg/kg. The mean dose (range) for the 21-day interval was 545 mg/kg (429 - 689 mg/kg); the mean dose (range) for the 28-day interval was 521 mg/kg (316- 800 mg/kg). Subjects received a total of 368 infusions of GAMMAPLEX 5%. The maximum infusion rate allowed during this clinical trial was 0.08 mL/kg/min (4 mg/kg/min).

The efficacy analysis was based on the annual rate of acute serious bacterial infections (SABIs), defined as pneumonia, bacteremia/septicemia, osteomyelitis/septic arthritis, visceral abscess, and bacterial meningitis, per subject per year^15. Other efficacy analyses were based on the annual rate of infections, antibiotic use, days 'Absence from school/nursery' and days of hospitalization.

During the 12-month clinical trial period, two serious acute bacterial infections occurred in any subject with an onset date between the first infusion of GAMMAPLEX 5% and the first follow-up visit, inclusive. Thus, the mean event rate of serious, acute, bacterial infections per year was 0.09 (with an upper 1-sided 99% confidence interval of 0.36).

Table 8: Summary of pediatric Efficacy Results in Pediatric subjects with PI
Clinical Analyses for Efficacy | Number of Subjects | 25
Clinical Analyses for Efficacy | Total Number of Subject Days | 8557
Infections | Annual rate of confirmed serious acute bacterial infections [Defined as pneumonia, bacterial meningitis, bacteremia/septicemia, osteomyelitis/septic arthritis, and visceral abscess.] | 0.09/subject year [Upper 1-sided 99% confidence interval: 0.36]
Infections | Annual rate of other infections (median) | 3.08 infections/subject year
Antibiotic use (therapeutic) | Number of subjects (%) | 21 (84%)
Antibiotic use (therapeutic) | Annual rate | 32.3 days/subject year
'Absence from school/nursery' | Number of subjects (%) | 16 (64%)
'Absence from school/nursery' | Number of days (%) | 102 (1.19%)
'Absence from school/nursery' | Annual rate | 4.2 days/subject year
Hospitalization | Number of subjects (%) | 3 (12%)
Hospitalization | Number of days (%) | 6 (0.07%)
Hospitalization | Annual rate | 0.3 days/subject year
Duration of exposure in all tables relating to the pediatric study was calculated as the difference between the date of the last visit (first follow-up visit) i.e. approximately 10-14 days following the last dose of GAMMAPLEX 5% and the date of the first GAMMAPLEX 5% infusion (plus one day).

14.2 Treatment of Chronic Immune Thrombocytopenic Purpura

In a Phase 3 multicenter, open-label clinical trial to evaluate the efficacy and safety of GAMMAPLEX 5% in chronic immune thrombocytopenic purpura, of the 35 subjects enrolled from various ethnic groups, 9 were male and 26 were female. The age range was between 6 and 69 years. Subjects received intravenous infusions on two consecutive days (1 course) and then observed for a further 30 days. Individuals were given the option of a further two courses of treatment (if required), where only safety variables were assessed. Doses of GAMMAPLEX 5% ranged from 482 to 1149 mg/kg on Day 1 and Day 2. The median total dose per subject was 2035 mg/kg. Subjects received a total of 94 infusions (48 treatment courses). All 35 subjects received at least one infusion of clinical trial drug, and all but one subject completed the first course of treatment.

The primary analysis was based on the platelet count achieved by Day 9 after the first course of treatment with GAMMAPLEX 5%, response being defined as a platelet count of 50 × 10^9/L or greater. Response to treatment on or before Day 9 was achieved by 29 of 35 subjects (82.9%), and the one-sided 97.5% lower confidence limit of the response rate was 66.4%, which met the a priori success criterion that required it to be greater than 60%.

Efficacy analyses included the duration of response, and changes in the incidences of bleeding or hemorrhage. At Day 32, the median (+ SD) platelet count (24 + [90] × 10^9/L) was still higher than the baseline value, and 11 of 33 subjects (33.3%) continued to show response of platelet counts of 50 × 10^9/L or greater. The median duration of platelet count response for the responders was 10 days.

Table 9: Median Platelet Count (Standard deviation) and Number and Percent of Subjects with a Platelet Count > 50 × 10^9/L during the clinical trial.
Number of days in clinical trial | Day 1 | Day 2 | Day 3 | Day 5 | Day 9 | Day 14 | Day 21 | Day 32
Median Platelet count (× 10^9/L) (Std Dev) | 12.0 (11.4) | 50.0 (36.4) | 93.0 (97.3) | 121.5 (151.9) | 100.5 (201.3) | 15.5 (113.0) | 30.0 (80.0) | 24.0 (89.9)
Number (n/N) and percent of subjects with a platelet count ≥ 50 ×10^9/L | 0/35 (0.0%) | 18/35 (51.4%) | 22/32 (68.8%) | 25/32 (78.1%) | 22/32 (68.8%) | 11/30 (36.7%) | 10/29 (34.5%) | 11/33 (33.3%)
GAMMAPLEX 5% infusions given on Days 1 and 2.

There was an increase in platelet counts for the majority of subjects, and an overall reduction in the manifestations of bleeding after treatment compared to baseline (Day 1). Petechiae, hematomas and gastrointestinal, pulmonary and genitourinary bleeds were all either reduced or absent by Day 32.

There were no thromboembolic episodes in the clinical trial; and vital signs, biochemical, hematological and virology tests did not reveal any unexpected pathophysiology or toxicity.

15 REFERENCES

1. Gupta N, Ahmed I, Nissel-Horowitz S, Patel D, Mehrotra B. Intravenous gammaglobulin-associated acute renal failure. Am J Hematol 2001; 66:151-152. 2. Dalakas MC. High-dose intravenous immunoglobulin and serum viscosity: risk of precipitating thromboembolic events. Neurology 1994; 44:223-226. 3. Gabor EP. Meningitis and skin reaction after intravenous immune globulin therapy. Ann Intern Med 1997; 127:1130. 4. Wilson JR, Bhoopalam N, Fisher M. Hemolytic anemia associated with intravenous immunoglobulin. Muscle Nerve 1997; 20:1142-1145. 5. Kessary-Shoham H, Levy Y, Shoenfeld Y, Lorber M, Gershon H. In vivo administration of intravenous immunoglobulin (IVIg) can lead to enhanced erythrocyte sequestration. J Autoimmun 1999; 13:129-135. 6. Kahwaji J, Barker E, Pepkowitz S, et al. Acute Hemolysis After High-Dose Intravenous Immunoglobulin Therapy in Highly HLA Sensitized Patients. Clin J Am Soc Nephrol 2009;4:1993-1997. 7. Daw Z, Padmore R, Neurath D, et al. Hemolytic transfusion reactions after administration of intravenous immune (gamma) globulin: A case series analysis. Transfusion 2008;48:1598-1601. 8. Rizk A, Gorson KC, Kenney L, Weinstein R. Transfusion-related acute lung injury after the infusion of IVIG. Transfusion 2001; 41:264-268. 9. Pierce LR, Jain N. Risks associated with the use of intravenous immunoglobulin. Trans Med Rev 2003; 17:241-251. 10. Siber GA, Werner BG, Halsey NA, Reid R, Almeido-Hill J, Garrett SC, Thompson C, Santosham M. Interference of immune globulin with measles and rubella immunization. J Pediatr 1993; 122:204-211. 11. Salisbury D, Ramsay M, Noakes K, eds. Immunisation against infectious disease. The Stationery Office (TSO), London: UK Department of Health, 2009; p426. 12. Sidiropoulos D, Herrmann U, Morell A, von Muralt G, Barandun S. Transplacental passage of intravenous immunoglobulin in the last trimester of pregnancy. J Pediatr 1986; 109:505-508. 13. Wood P, Stanworth S, Burton J, Jones A, Peckham DG, Chapel H. Recognition, clinical diagnosis and management of patients with primary antibody deficiencies: a systematic review. Clin Exp Immunol 2007; 149:410-423. 14. Simon H, Späth P. IVIG – Mechanisms of action. Allergy 2003; 58(7):543-52. 15. Center for Biologics Evaluation and Research. Guidance for Industry: Safety, Efficacy, and Pharmacokinetic Studies to Support Marketing of Immune Globulin Intravenous (Human) as Replacement Therapy for Primary Humoral Immunodeficiency. Rockville, MD: U.S. Department of Health and Human Services, Food and Drug Administration; July, 2008.

16 HOW SUPPLIED/STORAGE AND HANDLING

GAMMAPLEX 5% is supplied in a single use, clear Type II glass bottle, closed with a stopper and oversealed with a tamper-evident cap.

The components used in the packaging for GAMMAPLEX 5% are not made with natural rubber latex.

The following presentations of GAMMAPLEX 5% are available:

Grams and Fill Size | Carton NDC Number | Vial NDC Number
5 g in 100 mL | 64208-8234-6 | 64208-8234-2
10 g in 200 mL | 64208-8234-7 | 64208-8234-3
20 g in 400 mL | 64208-8234-8 | 64208-8234-4

Each vial has a label with a peel-off strip showing the product name and batch number.

STORAGE AND HANDLING

When stored between 2 °C [35.6 °F] and 25 °C [77 °F], GAMMAPLEX 5% has a shelf-life of 36 months.

Keep GAMMAPLEX 5% in its original carton to protect it from light.

Do not freeze.

17 PATIENT COUNSELING INFORMATION

Inform patients to immediately report the following signs and symptoms to their healthcare professional:

- Decreased urine output, sudden weight gain, fluid retention/edema, and/or shortness of breath [see Warnings and Precautions (5.1)].
- Acute chest pain, shortness of breath, leg pain, and swelling of the legs/feet [see Warnings and Precautions (5.2)].
- Severe headache, neck stiffness, drowsiness, fever, sensitivity to light, painful eye movements, nausea and vomiting [see Warnings and Precautions (5.5)].
- Increased heart rate, fatigue, yellowing of skin or eyes, dark-colored urine [see Warnings and Precautions (5.6)].
- Trouble breathing, chest pain, blue lips or extremities, fever [see Warnings and Precautions (5.7)].

Inform patients that GAMMAPLEX 5% is made from human plasma and may contain infectious agents that can cause disease. While the risk that GAMMAPLEX 5% can transmit an infection has been reduced by screening plasma donors for prior exposure, testing donated plasma, and inactivating or removing certain viruses during manufacturing, patients should report any symptoms that concern them [see Warnings and Precautions (5.9)].

Inform patients that GAMMAPLEX 5% can interfere with their immune response to live viral vaccines (e.g. measles, mumps, and rubella), and instruct patients to notify their healthcare professional of this potential interaction when they are receiving vaccinations [see Drug Interactions (7)].

Instruct patients to immediately report symptoms of thrombosis. These symptoms may include: pain and/or swelling of an arm or leg with warmth over the affected area, discoloration of an arm or leg, unexplained shortness of breath, chest pain or discomfort that worsens on deep breathing, unexplained rapid pulse, numbness or weakness on one side of the body.

Manufactured by:
Bio Products Laboratory Ltd.,
Elstree,
WD6 3BX.
United Kingdom.

Marketed by:
Kedrion Biopharma, Inc.,
Parker Plaza,
400 Kelby Street,
Fort Lee, NJ 07024,
United States.

US License No. 1811

PRINCIPAL DISPLAY PANEL - 100 mL Bottle Label

NDC: 64208-8234-2

Immune Globulin Intravenous (Human)
solution for infusion

Gammaplex® 5%

5 g

100 mL

- For intravenous use only
- Directions for use: Read enclosed package
  insert before use. Use immediately after
  piercing cap
- Do not freeze

- Do not use unless clear and free
  from deposit

- Maximum infusion rate 0.08 mL/kg per minute
- Store between 2°C and 25°C (35.6°F and 77°F)
  protected from light

Rx only

VSCUS7L

Marketed by: Kedrion Biopharma, Inc,
400 Kelby St., Fort Lee, NJ 07024, United States

Manufactured by: Bio Products Laboratory Ltd.,
Elstree, Borehamwood, WD6 3BX. U.K.

U.S. License No. 1811

PRINCIPAL DISPLAY PANEL - 100 mL Bottle Carton

NDC: 64208-8234-6

Immune Globulin
Intravenous (Human)
Gammaplex® 5%

5 g

solution for infusion

For intravenous use only

Rx only

1 vial

100 mL

Bio Products Laboratory

PRINCIPAL DISPLAY PANEL - 200 mL Bottle Label

NDC: 64208-8234-3

Immune Globulin Intravenous (Human)
solution for infusion

Gammaplex® 5%

10 g

200 mL

- For intravenous use only
- Directions for use:
  Read enclosed package
  insert before use. Use
  immediately after piercing cap

- Do not freeze
- Do not use unless clear
  and free from deposit

- Maximum infusion rate 0.08 mL/kg
  per minute
- Store between 2°C and 25°C
  (35.6°F and 77°F) protected
  from light

Rx only

VSAUS7L

Marketed by: Kedrion Biopharma, Inc,
400 Kelby St., Fort Lee, NJ 07024, United States

Manufactured by: Bio Products Laboratory Ltd.,
Elstree, Borehamwood, WD6 3BX. U.K.

U.S. License No. 1811

PRINCIPAL DISPLAY PANEL - 200 mL Bottle Carton

NDC 64208-8234-7

Immune Globulin
Intravenous (Human)
Gammaplex® 5%

10 g

solution for infusion

For intravenous use only

Rx only

1 vial

200 mL

Bio Products Laboratory

PRINCIPAL DISPLAY PANEL - 400 mL Bottle Label

NDC: 64208-8234-4

Immune Globulin Intravenous (Human)
solution for infusion

Gammaplex® 5%

20 g

400 mL

- For intravenous use only
- Directions for use:
  Read enclosed package
  insert before use. Use
  immediately after piercing cap

- Do not freeze
- Do not use unless clear
  and free from deposit

- Maximum infusion rate 0.08 mL/kg
  per minute
- Store between 2°C and 25°C
  (35.6°F and 77°F) protected
  from light

Rx only

VSBUS8L

Marketed by: Kedrion Biopharma, Inc,
400 Kelby St., Fort Lee, NJ 07024, United States

Manufactured by: Bio Products Laboratory Ltd.,
Elstree, Borehamwood, WD6 3BX. U.K.

U.S. License No. 1811

PRINCIPAL DISPLAY PANEL - 400 mL Bottle Carton

NDC 64208-8234-8

Immune Globulin
Intravenous (Human)
Gammaplex® 5%

20 g

solution for infusion

For intravenous use only

Rx only

1 vial

400 mL

Bio Products Laboratory